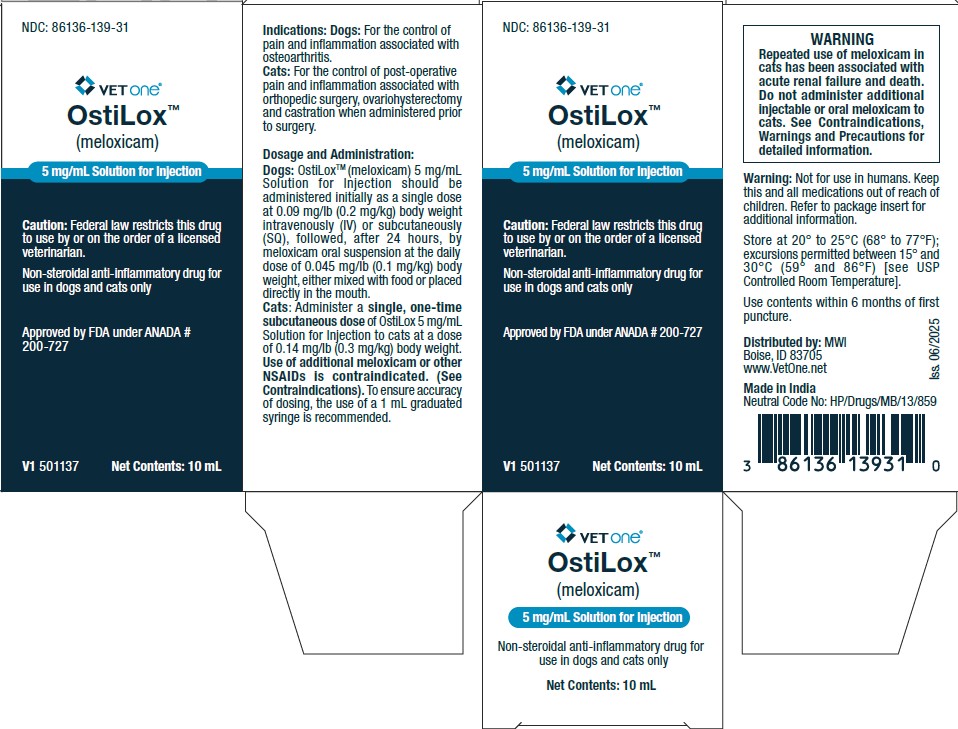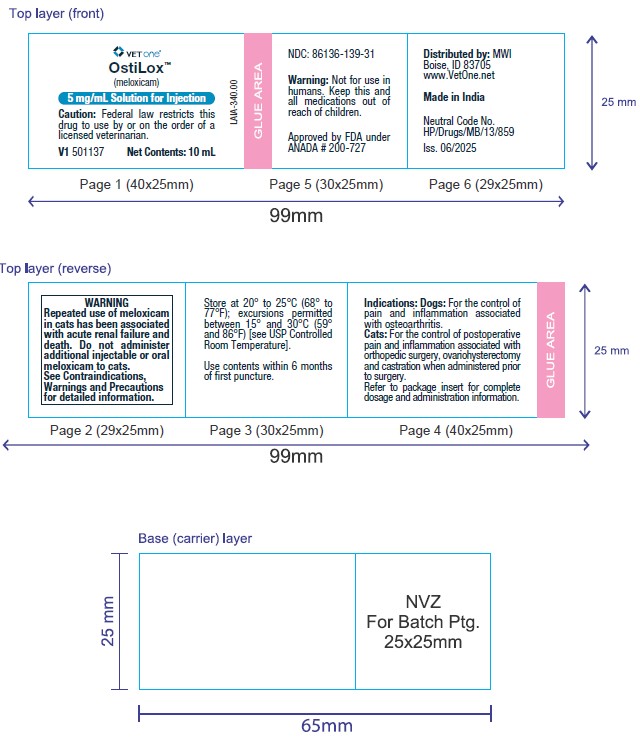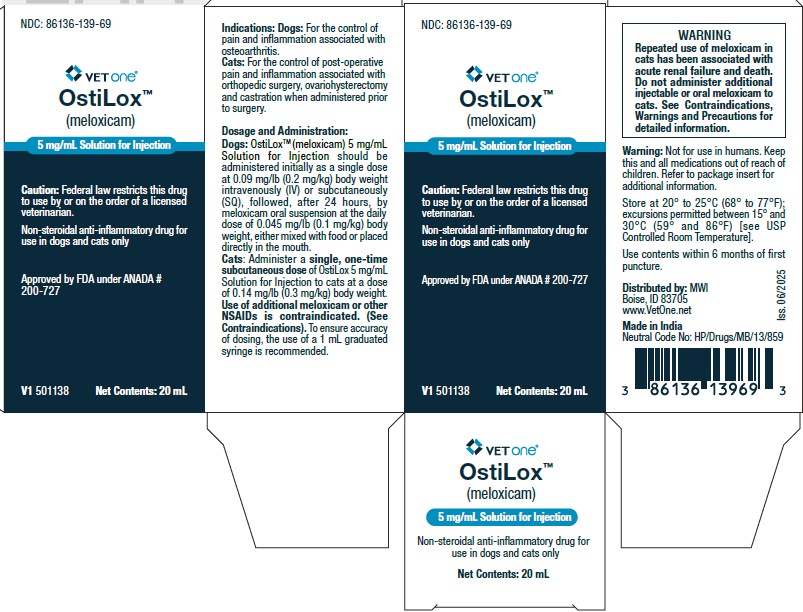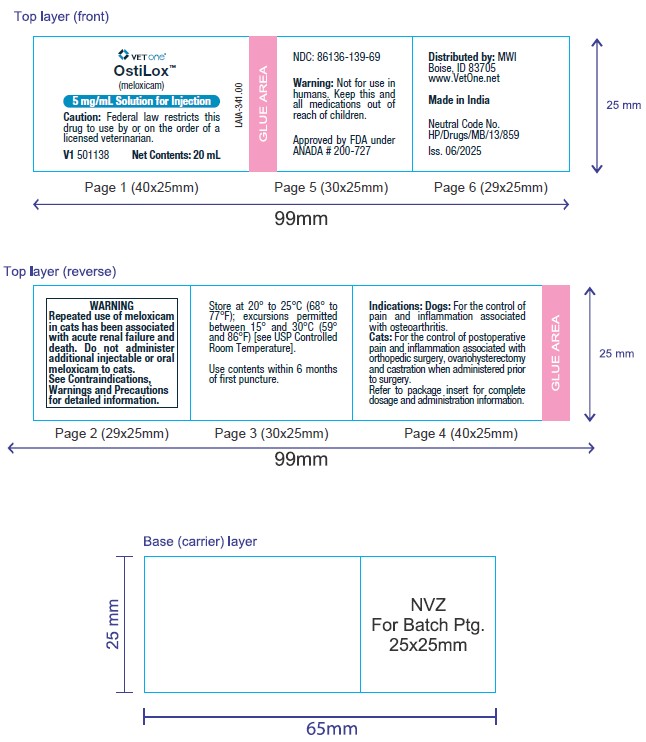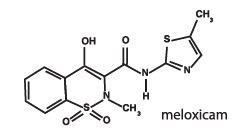 DRUG LABEL: OstiLox
NDC: 86136-139 | Form: INJECTION, SOLUTION
Manufacturer: MWI/Vetone
Category: animal | Type: Prescription Animal Drug Label
Date: 20250729

ACTIVE INGREDIENTS: MELOXICAM 5 mg/1 mL

OstiLox™
(meloxicam)
5 mg/mL Solution for Injection

Package Insert for Dogs

Non-steroidal anti-inflammatory drug for use in dogs and cats only

Caution:

Federal law restricts this drug to use by or on the order of a licensed veterinarian.

BOXED WARNING

WARNING: Repeated use of meloxicam in cats has been associated with acute renal failure and death. Do not administer additional injectable or oral meloxicam to cats. See Contraindications, Warnings, and Precautions for detailed information.

Description:

Meloxicam is a non-steroidal anti-inflammatory drug (NSAID) of the oxicam class. Each mL of this sterile product for injection contains meloxicam 5.0 mg, alcohol 15%, glycofurol 10%, poloxamer 188 5%, sodium chloride 0.6%, glycine 0.5% and meglumine 0.3%, in water for injection, pH adjusted with sodium hydroxide and hydrochloric acid.

Indications:

Dogs: OstiLoxTM (meloxicam) 5 mg/mL Solution for Injection is indicated in dogs for the control of pain and inflammation associated with osteoarthritis.

Dosage and Administration:

Carefully consider the potential benefits and risk of OstiLox and other treatment options before deciding to use OstiLoxTM (meloxicam) 5 mg/mL Solution for Injection. Use the lowest effective dose for the shortest duration consistent with individual response.

Dogs: OstiLox (meloxicam) 5 mg/mL Solution for Injection should be administered initially as a single dose at 0.09 mg/lb (0.2 mg/kg) body weight intravenously (IV) or subcutaneously (SQ), followed, after 24 hours, by meloxicam oral suspension at the daily dose of 0.045 mg/lb (0.1 mg/kg) body weight, either mixed with food or placed directly in the mouth.

Contraindications:

Dogs with known hypersensitivity to meloxicam should not receive OstiLox (meloxicam) 5 mg/mL Solution for Injection.

Warnings:

Not for use in humans. Keep this and all medications out of reach of children. Consult a physician in case of accidental ingestion by humans. For IV or SQ injectable use in dogs. All dogs should undergo a thorough history and physical examination before administering any NSAID. Appropriate laboratory testing to establish hematological and serum biochemical baseline data is recommended prior to, and periodically during use of any NSAID in dogs.

Owner should be advised to observe their dogs for signs of potential drug toxicity.

Precautions:

The safe use of OstiLox (meloxicam) 5 mg/mL Solution for Injection in dogs younger than 6 months of age, dogs used for breeding, or in pregnant or lactating bitches has not been evaluated. Meloxicam is not recommended for use in dogs with bleeding disorders, as safety has not been established in dogs with these disorders. Safety has not been established for intramuscular (IM) administration in dogs. When administering OstiLox (meloxicam) 5 mg/mL Solution for Injection, use a syringe of appropriate size to ensure precise dosing. As a class, cyclo-oxygenase inhibitory NSAIDs may be associated with gastrointestinal, renal and hepatic toxicity. Sensitivity to drug-associated adverse events varies with the individual patient. Dogs that have experienced adverse reactions from one NSAID may experience adverse reactions from another NSAID. Patients at greatest risk for renal toxicity are those that are dehydrated, on concomitant diuretic therapy, or those with existing renal, cardiovascular, and/or hepatic dysfunction. Concurrent administration of potentially nephrotoxic drugs should be carefully approached. NSAIDs may inhibit the prostaglandins that maintain normal homeostatic function. Such anti-prostaglandin effects may result in clinically significant disease in patients with underlying or preexisting disease that has not been previously diagnosed.

Since NSAIDs possess the potential to induce gastrointestinal ulcerations and/or perforations, concomitant use with other anti-inflammatory drugs, such as NSAIDs or corticosteroids, should be avoided. If additional pain medication is needed after the administration of the total daily dose of meloxicam oral suspension, a non-NSAID or noncorticosteroid class of analgesia should be considered. The use of another NSAID is not recommended. Consider appropriate washout times when switching from corticosteroid use or from one NSAID to another in dogs. The use of concomitantly protein-bound drugs with OstiLox (meloxicam) 5 mg/mL Solution for Injection has not been studied in dogs. Commonly used protein-bound drugs include cardiac, anticonvulsant and behavioral medications. The influence of concomitant drugs that may inhibit metabolism of OstiLox (meloxicam) 5 mg/mL Solution for Injection has not been evaluated. Drug compatibility should be monitored in patients requiring adjunctive therapy. The effect of cyclo-oxygenase inhibition and the potential for thromboembolic occurrence or a hypercoagulable state has not been studied.

Adverse Reactions:

Dogs: A field study involving 224 dogs was conducted. Based on the results of this study, GI abnormalities (vomiting, soft stools, diarrhea, and inappetence) were the most common adverse reactions associated with the administration of meloxicam. The following table lists adverse reactions and the numbers of dogs that experienced them during the study. Dogs may have experienced more than one episode of the adverse reaction during the study.

Adverse Reactions Observed During Field Study
Clinical Observation | Meloxicam (n=109) | Placebo (n=115)
Vomiting | 31 | 15
Diarrhea/Soft Stool | 15 | 11
Inappetance | 3 | 0
Bloody Stool | 1 | 0

In foreign suspected adverse drug reaction (SADR) reporting, adverse reactions related to meloxicam administration included: auto-immune hemolytic anemia (1 dog), thrombocytopenia (1 dog), polyarthritis (1 dog), nursing puppy lethargy (1 dog), and pyoderma (1 dog).

Post-Approval Experience (Rev. 2009):

The following adverse reactions are based on post-approval adverse drug event reporting. The categories are listed in decreasing order of frequency by body system:
Gastrointestinal: vomiting, diarrhea, melena, gastrointestinal ulceration
Urinary: azotemia, elevated creatinine, renal failure
Neurological/Behavioral: lethargy, depression
Hepatic: elevated liver enzymes
Dermatologic: pruritus

Death has been reported as an outcome of the adverse events listed above. Acute renal failure and death have been associated with the use of meloxicam in cats.

CONTACT INFORMATION:

To report suspected adverse drug events, for technical assistance or to obtain a copy of the SDS, contact Felix Pharmaceuticals Private Limited at 1-833-571-1525.
For additional information about adverse drug experience reporting for animal drugs, contact FDA at 1-888-FDA-VETS or online at www.fda.gov/reportanimalae

Information for Dog Owners:

Meloxicam, like other NSAIDs, is not free from adverse reactions. Owners should be advised of the potential for adverse reactions and be informed of the clinical signs associated with NSAID intolerance. Adverse reactions may include vomiting, diarrhea, lethargy, decreased appetite and behavioral changes. Dog owners should be advised when their pet has received a meloxicam injection. Dog owners should contact their veterinarian immediately if possible adverse reactions are observed, and dog owners should be advised to discontinue OstiLox therapy.

Clinical Pharmacology:

Meloxicam has nearly 100% bioavailability when administered orally or after subcutaneous injection in dogs. The terminal elimination half-life after a single dose is estimated to be approximately 24 hrs (+/- 30%) in dogs regardless of route of administration. Drug bioavailability, volume of distribution, and total systemic clearance remain constant up to 5 times the recommended dose for use in dogs. However, there is some evidence of enhanced drug accumulation and terminal elimination half-life prolongation when dogs are dosed for 45 days or longer.

Peak drug concentrations of 0.734 mcg/mL can be expected to occur within 2.5 hours following a 0.2 mg/kg subcutaneous injection in dogs. Based upon intravenous administration in Beagle dogs, the meloxicam volume of distribution in dogs (Vdλ) is approximately 0.32 L/kg and the total systemic clearance is 0.01 L/hr/kg. The drug is 97% bound to canine plasma proteins.

Effectiveness:

Dogs: The effectiveness of meloxicam injection was demonstrated in a field study involving a total of 224 dogs representing various breeds, all diagnosed with osteoarthritis. This placebo-controlled, masked study was conducted for 14 days. Dogs received a subcutaneous injection of 0.2 mg/kg meloxicam injection on day 1. The dogs were maintained on 0.1 mg/kg oral meloxicam from days 2 through 14. Variables evaluated by veterinarians included lameness, weight-bearing, pain on palpation, and overall improvement. Variables assessed by owners included mobility, ability to rise, limping, and overall improvement. In this field study, dogs showed clinical improvement with statistical significance after 14 days of meloxicam treatment for all variables.

Animal Safety:

Dogs: 3 Day Target Animal Safety Study - In a three day safety study, meloxicam injection was administered intravenously to Beagle dogs at 1, 3, and 5 times the recommended dose (0.2, 0.6 and 1.0 mg/kg) for three consecutive days. Vomiting occurred in 1 of 6 dogs in the 5X group. Fecal occult blood was detected in 3 of 6 dogs in the 5X group. No clinically significant hematologic changes were seen, but serum chemistry changes were observed. Serum alkaline phosphatase (ALP) was significantly increased in one 1X dog and two of the 5X dogs.
One dog in the 5X group had a steadily increasing GGT over 4 days, although the values remained within the reference range. Decreases in total protein and albumin occurred in 2 of 6 dogs in the 3X group and 3 of 6 dogs in the 5X group. Increases in blood urea nitrogen (BUN) occurred in 3 of 6 dogs in the 1X group, 2 of 6 dogs in the 3X group and 2 of 6 dogs in the 5X group. Increased creatinine occurred in 2 dogs in the 5X group. Increased urine protein excretion was noted in 2 of 6 dogs in the control group, 2 of 6 dogs in the 1X group, 2 of 6 dogs in the 3X group, and 5 of 6 dogs in the 5X group. Two dogs in the 5X group developed acute renal failure by Day 4. Bicarbonate levels were at or above normal levels in 1 of the 3X dogs and 2 of the 5X dogs.

Histological examination revealed gastrointestinal lesions ranging from superficial mucosal hemorrhages and congestion to erosions. Mesenteric lymphadenopathy was identified in 2 of 6 dogs in the 1X group, 4 of 6 dogs in the 3X group, and 5 of 6 dogs in the 5X group. Renal changes ranged from dilated medullary and cortical tubules and inflammation of the interstitium, to necrosis of the tip of the papilla in 2 of 6 dogs in the 1X group, 2 of 6 dogs in the 3X group, and 4 of 6 dogs in the 5X group.

Injection Site Tolerance - Meloxicam injection was administered once subcutaneously to Beagle dogs at the recommended dose of 0.2 mg/kg and was well-tolerated by the dogs. Pain upon injection was observed in one of eight dogs treated with meloxicam. No pain or inflammation was observed post-injection. Long term use of meloxicam injection in dogs has not been evaluated.

Effect on Buccal Mucosal Bleeding Time (BMBT) - Meloxicam (0.2 mg/kg) and placebo (0.4 mL/kg) were administered as single intravenous injections to 8 female and 16 male Beagle dogs. There was no statistically significant difference (p>0.05) in the average BMBT between the two groups.

Storage Information:

Store at 20° to 25°C (68° to 77°F); excursions permitted between 15° and 30°C (59° and 86°F) [see USP Controlled Room Temperature].

Use contents within 6 months of first puncture.

How Supplied:

OstiLox (meloxicam) 5 mg/mL Solution for Injection: 10 mL vial and 20 mL vial

NDC no. 86136-139-31 - 10 mL

NDC no. 86136-139-69 - 20 mL

Approved by FDA under ANADA # 200 - 727
Distributed by:
MWI
Boise, ID 83705
www.VetOne.net
Made in India
Neutral Code No. HP/Drugs/MB/13/859
Iss. 06/2025

OstiLoxTM (meloxicam) 5mg/mL Solution for Injection

Package Insert for Cats

Non-steroidal anti-inflammatory drug for use in dogs and cats only

Caution:

Federal law restricts this drug to use by or on the order of a licensed veterinarian.

BOXED WARNING

WARNING: Repeated use of meloxicam in cats has been associated with acute renal failure and death. Do not administer additional injectable or oral meloxicam to cats. See Contraindications, Warnings, and Precautions for detailed information.

Description:

Meloxicam is a non-steroidal anti-inflammatory drug (NSAID) of the oxicam class. Each mL of this sterile product for injection contains meloxicam 5.0 mg, alcohol 15%, glycofurol 10%, poloxamer 188 5%, sodium chloride 0.6%, glycine 0.5% and meglumine 0.3%, in water for injection, pH adjusted with sodium hydroxide and hydrochloric acid.

Indications:

Cats: For the control of postoperative pain and inflammation associated with orthopedic surgery, ovariohysterectomy and castration when administered prior to surgery.

Dosage and Administration:

Carefully consider the potential benefits and risk of OstiLox and other treatment options before deciding to use OstiLox 5 mg/mL Solution for Injection. Use the lowest effective dose for the shortest duration consistent with individual response.

Cats: Administer a single, one-time subcutaneous dose of OstiLoxTM (meloxicam) 5 mg/mL Solution for Injection to cats at a dose of 0.14 mg/lb (0.3 mg/kg) body weight. Use of additional meloxicam or other NSAIDs is contraindicated. (See Contraindications). To ensure accuracy of dosing, the use of a 1 mL graduated syringe is recommended.

Contraindications:

Cats with known hypersensitivity to meloxicam should not receive OstiLox 5 mg/mL Solution for Injection. Additional doses of meloxicam or other NSAIDs in cats are contraindicated, as no safe dosage for repeated NSAID administration has been established (See Animal Safety). Do not use meloxicam in cats with pre-existing renal dysfunction.

Warnings:

Not for use in humans. Keep this and all medications out of reach of children. Consult a physician in case of accidental ingestion by humans. For subcutaneous (SQ) injectable use in cats. Do not use IV in cats.

Do not administer a second dose of meloxicam.
Do not follow the single, one-time dose of meloxicam with any other NSAID.
Do not administer meloxicam oral suspension following the single, one-time injectable dose of meloxicam.

When administering any NSAID, appropriate laboratory testing to establish hematological and serum biochemical baseline data is recommended prior to use in dogs and cats. All cats should undergo a thorough history and physical examination before administering meloxicam. Do not repeat the single, one-time dose of meloxicam in cats.

Owner should be advised to observe their cats for signs of potential drug toxicity.

Precautions:

The safe use of OstiLox 5 mg/mL Solution for Injection in cats younger than 4 months of age, cats used for breeding, or in pregnant or lactating queens has not been evaluated.

Meloxicam is not recommended for use in cats with bleeding disorders, as safety has not been established in cats with these disorders. Safety has not been established for intravenous (IV) or intramuscular (IM) use in cats. When administering OstiLox 5 mg/mL Solution for Injection, use a syringe of appropriate size to ensure precise dosing.

As a class, cyclo-oxygenase inhibitory NSAIDs may be associated with gastrointestinal, renal, and hepatic toxicity. Sensitivity to drug-associated adverse events varies with the individual patient. Cats that have experienced adverse reactions from one NSAID may experience adverse reactions from another NSAID. NSAIDs may inhibit the prostaglandins that maintain normal homeostatic function. Such anti-prostaglandin effects may result in clinically significant disease in patients with underlying or pre-existing disease that has not been previously diagnosed.

Patients at greatest risk for adverse events are those that are dehydrated, on concomitant diuretic therapy, or those with existing renal, cardiovascular, and/or hepatic dysfunction. Concurrent administration of potentially nephrotoxic drugs should be carefully approached and monitored. Anesthetic drugs may affect renal perfusion; approach concomitant use of anesthetics and NSAIDs cautiously. Appropriate monitoring procedures should be employed during all surgical procedures. The use of perioperative parenteral fluids is recommended to decrease potential renal complications when using NSAIDs. If additional pain medication is needed after the single one-time dose of meloxicam, a non-NSAID class of analgesic may be necessary.

In one study^1, one cat in each NSAID treatment group had increased intraoperative hemorrhage.

Since NSAIDs possess the potential to induce gastrointestinal ulcerations and/or gastrointestinal perforation, concomitant use of meloxicam with other anti-inflammatory drugs, such as NSAIDs or corticosteroids, should be avoided.

Consider appropriate washout times when switching from corticosteroid use to meloxicam in cats. As a single use product in cats, meloxicam should not be followed by additional NSAIDs or corticosteroids.

The use of concomitantly protein-bound drugs with OstiLox 5 mg/mL Solution for Injection has not been studied in cats. Commonly used protein-bound drugs include cardiac, anticonvulsant and behavioral medications. The influence of concomitant drugs that may inhibit metabolism of OstiLox 5 mg/mL Solution for Injection has not been evaluated. Drug compatibility should be monitored in patients requiring adjunctive therapy. The effect of cyclo-oxygenase inhibition and the potential for thromboembolic occurrence or a hypercoagulable state has not been studied.

Adverse Reactions:

Cats: A field study involving 138 cats was conducted. Of the 72 cats receiving meloxicam injection, six cats (8.3%) experienced post-treatment elevated serum blood urea nitrogen (BUN) levels. The pre-treatment values were in the normal range. Of the 66 cats in the butorphanol treatment group, no cats experienced post-treatment elevated serum blood urea nitrogen levels. Nine cats (12.5%) receiving meloxicam injection had post-treatment anemia. Pre-treatment, these cats all had hematocrit and hemoglobin values in the normal range. Four cats (6.1%) in the butorphanol treatment group had post-treatment anemia. All but one cat, who had a mild anemia pre-treatment (hematocrit = 21% and hemoglobin = 7.0 g/dL) had normal pre-treatment values. Twenty-four hours after the injection with meloxicam injection, one cat experienced pain upon palpation of the injection site.

Foreign Experience:

Repeated use in cats has been associated with acute renal failure and death. In studies used for the foreign approval of meloxicam injection in cats, lethargy, vomiting, inappetance, and transient pain immediately after injection were noted. Diarrhea and fecal occult blood have also been reported.

Post-Approval Experience (Rev. 2009):

The following adverse reactions are based on post-approval adverse drug event reporting. The categories are listed in decreasing order of frequency by body system:
Urinary: azotemia, elevated creatine, elevated phosphorus, renal failure
Gastrointestinal: anorexia, vomiting, diarrhea
Neurologic/Behavioral: lethargy, depression
Hematologic: anemia

Death has been reported as an outcome of the adverse events listed above. Acute renal failure and death have been associated with the use of meloxicam in cats.

CONTACT INFORMATION:

To report suspected adverse drug events, for technical assistance or to obtain a copy of the SDS, contact Felix Pharmaceuticals Private Limited at 1-833-571-1525.
For additional information about adverse drug experience reporting for animal drugs, contact FDA at 1-888-FDA-VETS or online at www.fda.gov/reportanimalae

Information For Cat Owners:

Meloxicam, like other NSAIDs, is not free from adverse reactions. Owners should be advised of the potential for adverse reactions and be informed of the clinical signs associated with NSAID intolerance. Adverse reactions may include vomiting, diarrhea, lethargy, decreased appetite and behavioral changes.
Cat owners should be advised when their pet has received a OstiLoxTM (meloxicam) 5 mg/mL Solution for Injection. Cat owners should contact their veterinarian immediately if possible adverse reactions are observed.

Clinical Pharmacology:

Meloxicam has nearly 100% bioavailability after subcutaneous injection in cats. The terminal elimination half life after a single dose is estimated to be approximately 15 hrs (+/-10%) in cats. Peak drug concentrations of 1.1 mcg/mL can be expected to occur within 1.5 hours following a 0.3 mg/kg subcutaneous injection in cats. The volume of distribution (Vdλ) in cats is approximately 0.27 L/kg, with an estimated total systemic clearance of 0.013 L/hr/kg. The drug is 97% bound to feline plasma proteins.

Effectiveness:

Cats: The effectiveness of meloxicam injection was demonstrated in a masked field study involving a total of 138 cats representing various breeds. This study used butorphanol as an active control. Cats received either a single subcutaneous injection of 0.3 mg/kg meloxicam injection or 0.4 mg/kg butorphanol prior to onychectomy, either alone or in conjunction with surgical neutering. All cats were premedicated with acepromazine, induced with propofol and maintained on isoflurane. Pain assessment variables evaluated by veterinarians included additional pain intervention therapy, gait/lameness score, analgesia score, sedation score, general impression score, recovery score, and visual analog scale score. Additionally, a cumulative pain score, which was the summation of the analgesia, sedation, heart rate and respiratory rate scores was evaluated. A palpometer was used to quantify the pain threshold.

A substantial number of cats required additional intervention in the 0-24 hour postsurgical period, with the majority of these interventions taking place within the first hour. Therefore, the percentage of cats in each group that received one or more interventions was designated as the primary assessment variable. Approximately half of the cats in each group received a pain intervention as a result of the first (time 0) post-surgical evaluation, i.e., extubation. At this point, the need to provide a pain intervention was not statistically significant between the two groups (p=0.7215). However, the median number of interventions was one per cat in the meloxicam group and two per cat in the butorphanol group and this difference was statistically significant (p=0.0021). The statistical evaluation supports the conclusion that the meloxicam test article is non-inferior to the butorphanol active control. Forty-eight of the 72 cats in the meloxicam group received one or more interventions (66.7%), and 47 of 66 cats in the butorphanol group received one or more interventions (71.2%). The number of interventions administered to the meloxicam group was less than the butorphanol group at 1, 3, 5, 8, 12, and 24 hours post-surgery.

Cats receiving meloxicam injection showed improvement in the pain assessment variables.

Animal Safety:

Cats: 3 Day Target Animal Safety Study - In a three day safety study, subcutaneous meloxicam injection administration to healthy cats at up to 1.5 mg/kg (5X the recommended dose) resulted in vomiting in three cats (1 of 6 control cats and 2 of 6 cats in 5X) and loose stools in four cats (2 of 6 control cats and 2 of 6 cats in 5X). Fecal occult blood was detected in ten of the twenty four cats, including two cats in the control group. This was not a dose-related event.

Clinically significant hematologic changes seen included increased PT and APTT in two cats (1 of 6 control cats and 1 of 6 cats in 5X), and elevated white blood cell counts in cats having renal or GI tract lesions. Serum chemistry changes observed included decreased total protein in four of 24 cats (1 of 6 cats in 1X, 2 of 6 cats in 3X and 1 of 6 cats in 5X), concomitant increases in blood urea nitrogen (BUN) and creatinine values in 2 of 6 cats in 5X.

Histological examination revealed gastrointestinal lesions ranging from inflammatory cell infiltration of the mucosa of the GI tract to erosions. Mesenteric lymphadenopathy was identified in 1 of 6 cats in 1X. Renal changes ranged from dilated medullary (2 of 6 cats in 1X, 1 of 6 cats in 3X, and 1 of 6 cats in 5X) and cortical (3 of 6 cats in 1X, 1 of 6 cats in 3X, and 3 of 6 cats in 5X) tubules and inflammation (2 of 6 cats in 1X, 2 of 6 cats in 3X, and 2 of 6 cats in 5X) or fibrosis (2 of 6 cats in 3X and 2 of 6 cats in 5X) of the interstitium to necrosis of the tip of the papilla (5 of 6 cats in 5X).

Subsequent oral dosing - In a nine day study with three treatment groups, meloxicam injection was given as a single subcutaneous injection using doses of 0 mg/kg (saline injection), 0.3 mg/kg and 0.6 mg/kg on Day 0. Meloxicam oral suspension, 1.5 mg/mL or saline was then administered orally once-daily at the same respective dose (0.3 or 0.6 mg/kg) for eight consecutive days. Clinical adverse reactions included vomiting, diarrhea, lethargy, and decreased food consumption in the treated groups, and one day of diarrhea in one control cat. The gross necropsy report includes observation of reddened GI mucosa in 3 of 4 cats in the 0.3 mg/kg group and 1 of 4 cats in the 0.6 mg/kg group. All saline-treated cats were normal. By Day 9, one cat in both the 0.3 mg/kg group and the 0.6 mg/kg group died and another cat in the 0.3 mg/kg group was moribund. The cause of death for these cats could not be determined, although the pathologist reported pyloric/duodenal ulceration in the cats in 0.6 mg/kg group. The safety studies demonstrate a narrow margin of safety.

Injection Site Tolerance - Histopathology of the injection sites revealed hemorrhage and inflammation, myofiber atrophy, panniculitis, fibrin deposition, and fibroblast proliferation. These findings were present in cats in all groups, with the 3X cats having the most present. No safe repeat dose has been established in cats.

Storage Information:

Store at 20° to 25°C (68° to 77°F); excursions permitted between 15° and 30°C (59° and 86°F) [see USP Controlled Room Temperature].

Use contents within 6 months of first puncture.

How Supplied:

OstiLox 5 mg/mL Solution for Injection: 10 mL vial and 20 mL vial

NDC no. 86136-139-31 - 10 mL

NDC no. 86136-139-69 - 20 mL

Reference:

1 Slingsby L.S., A.E. Waterman-Pearson. Comparison between meloxicam and carprofen for postoperative analgesia after feline ovariohysterectomy. Jour of Small Anim Pract (2002)43:286-289.

Approved by FDA under ANADA # 200 - 727
Distributed by:
MWI
Boise, ID 83705
www.VetOne.net
Made in India
Neutral Code No. HP/Drugs/MB/13/859
Iss. 06/2025

Principal Display Panel-10 mL carton

NDC: 86136-139-31

OstiLoxTM

(meloxicam)

5mg/mL Solution for Injection

Caution: Federal law restricts this drug to use by or on the order of a licensed veterinarian.

Non-steroidal anti-inflammatory drug for use in dogs and cats only

Approved by FDA under ANADA # 200-727

Net Contents: 10 mL

Principal Display Panel-10 mL Vial Label

NDC: 86136-139-31

OstiLoxTM

(meloxicam)

5mg/mL Solution for Injection

Caution: Federal law restricts this drug to use by or on the order of a licensed veterinarian.

Approved by FDA under ANADA # 200-727

Net Contents: 10 mL

Principal Display Panel-20 mL carton

NDC: 86136-139-69

OstiLoxTM

(meloxicam)

5mg/mL Solution for Injection

Caution: Federal law restricts this drug to use by or on the order of a licensed veterinarian.

Non-steroidal anti-inflammatory drug for use in dogs and cats only

Approved by FDA under ANADA # 200-727

Net Contents: 20 mL

Principal Display Panel-20 mL Vial Label

NDC: 86136-139-69

OstiLoxTM

(meloxicam)

5mg/mL Solution for Injection

Caution: Federal law restricts this drug to use by or on the order of a licensed veterinarian.

Approved by FDA under ANADA # 200-727

Net Contents: 20 mL